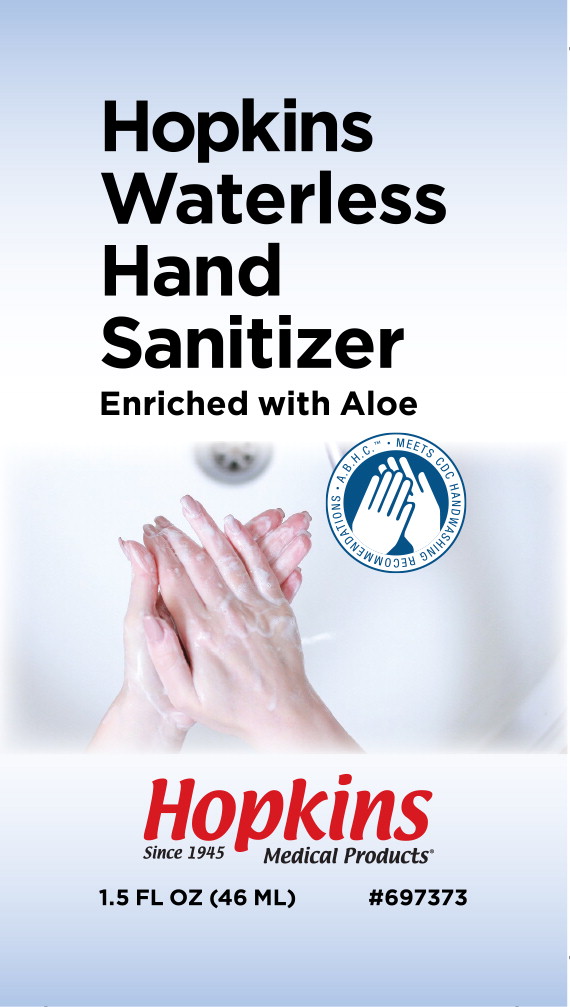 DRUG LABEL: Hand Sanitizer
NDC: 44662-1112 | Form: GEL
Manufacturer: Hopkins Medical
Category: otc | Type: HUMAN OTC DRUG LABEL
Date: 20200323

ACTIVE INGREDIENTS: alcohol 665 mL/1 L
INACTIVE INGREDIENTS: aloe vera leaf; CARBOMER HOMOPOLYMER TYPE C (ALLYL PENTAERYTHRITOL CROSSLINKED); D&C GREEN NO. 5; D&C YELLOW NO. 10; water; trolamine

Drug Facts

Active ingredient

Ethyl Alcohol 66.5%

Purpose

Antiseptic

Uses

- for handwashing to decrease bacteria on skin
- recommended for repeated use

Warnings

For external use only

Flammable, keep away from fire or flame

Do not use in the eyes. If this happens, rinse thoroughly with water.

Stop use and ask a doctor if irritation and redness develop and persists for more than 72 hours

Keep out of reach of children

If ingested get medical help or contact a Poison Control Center right away

Directions

- wet hands thoroughly with product
- allow to dry without wiping
- children under 6 should be supervised while using this product

Inactive ingredients

aloe vera, carbomer, D&C green #5, D&C yellow #10, fragrance, purified water, triethanolamine

Principal Display Panel – 1.5 fl. oz. Bottle Label

Hopkins
Waterless
Hand
Sanitizer

Enriched with Aloe

Hopkins

Medical Products

Since 1945

1.5 FL OZ (46 ML)

#697373